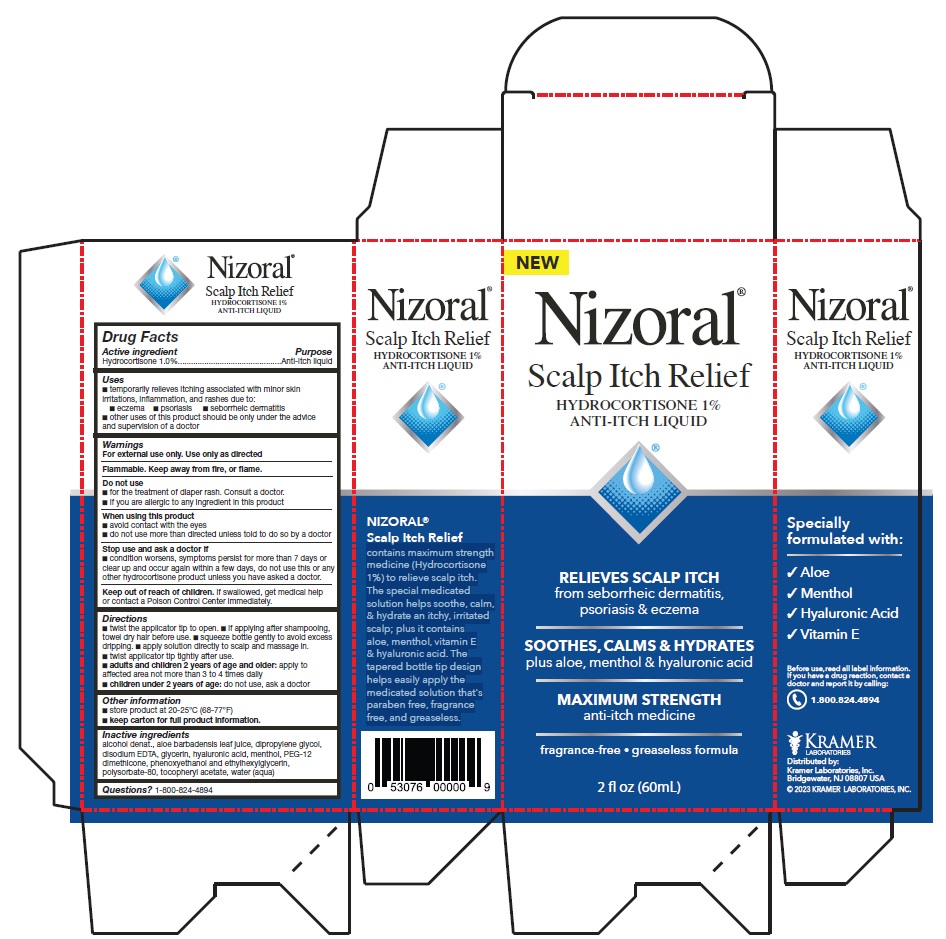 DRUG LABEL: Nizoral Scalp Itch Relief
NDC: 55505-222 | Form: SHAMPOO
Manufacturer: Kramer Laboratories
Category: otc | Type: HUMAN OTC DRUG LABEL
Date: 20251223

ACTIVE INGREDIENTS: Hydrocortisone 10 mg/1 mL
INACTIVE INGREDIENTS: Alcohol; Aloe; Dipropylene Glycol; Edetate Disodium Anhydrous; Glycerin; Hyaluronic Acid; Menthol, Unspecified Form; Peg-12 Dimethicone (300 Cst); Phenoxyethanol; Ethylhexylglycerin; Polysorbate 80; .Alpha.-Tocopherol Acetate; Water

Drug Facts

ACTIVE INGREDIENT

Active ingredient | Purpose
Hydrocortisone 1.0% | Anti-itch liquid

Uses

- temporarily relieves itching associated with minor skin irritations, inflammation, and rashes due to:
  - eczema
  - psoriasis
  - seborrheic dermatitis

- other uses of this product should be only under the advice and supervision of a doctor

Warnings
For external use only. Use only as directed

Flammable. Keep away from fire, or flame.

Do not use

- for the treatment of diaper rash. Consult a doctor.
- If you are allergic to any ingredient in this product

When using this product

- avoid contact with the eyes
- do not use more than directed unless told to do so by a doctor

Stop use and ask a doctor if

- condition worsens, symptoms persist for more than 7 days or clear up and occur again within a few days, do not use this or any other hydrocortisone product unless you have asked a doctor.

KEEP OUT OF REACH OF CHILDREN

Keep out of the reach of children. If swallowed, get medical help or contact a Poison Control Center immediately.

Directions

- twist the applicator tip to open.
- if applying after shampooing, towel dry hair before use.
- squeeze bottle gently to avoid excess dripping.
- apply solution directly to scalp and massage in.
- twist applicator tip tightly after use.
- adults and children 2 years of age and older: apply to affected area not more than 3 to 4 times daily
- children under 2 years of age: do not use, ask a doctor

Other information

- store product at 20-25°C (68-77°F)
- keep carton for full product information.

Inactive ingredients

alcohol denat., aloe barbadensis leaf juice, dipropylene glycol, disodium EDTA, glycerin, hyaluronic acid, menthol, PEG-12 dimethicone, phenoxyethanol and ethylhexylglycerin, polysorbate-80, tocopheryl acetate, water (aqua)

Questions? 1-800-824-4894

PRINCIPAL DISPLAY PANEL

Nizoral®
Scalp Itch Relief
HYDROCORTISONE 1%
ANTI-ITCH LIQUID
RELIEVES SCALP ITCH
from seborrheic dermatitis,
psoriasis & eczema
SOOTHES, CALMS & HYDRATES
plus aloe, menthol & hyaluronic acid
MAXIMUM STRENGTH
anti-itch medicine
fragrance-free • greaseless formula
2 fl oz (60mL)
NIZORAL®
Scalp Itch Relief
contains maximum strength
medicine (Hydrocortisone
1%) to relieve scalp itch.
The special medicated
solution helps soothe, calm,
& hydrate an itchy, irritated
scalp; plus it contains
aloe, menthol, vitamin E
& hyaluronic acid. The
tapered bottle tip design
helps easily apply the
medicated solution that's
paraben free, fragrance
free, and greaseless.
Specially
formulated with:
√ Aloe
√ Menthol
√ Hyaluronic Acid
√ Vitamin E
Before use, read all label information.
If you have a drug reaction, contact a
doctor and report it by calling:
1.800.824.4894
KRAMER
LABORITORIES
Distributed by:
Kramer Laboratories, Inc.
Bridgewater, NJ 08807 USA
© 2023 KRAMER LABORATORIES, INC.